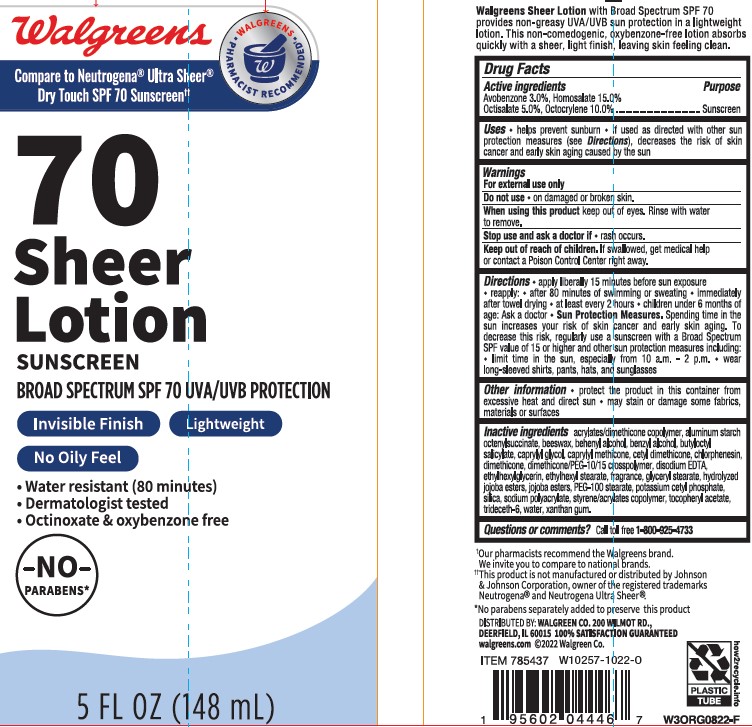 DRUG LABEL: Walgreens 70 Sheer Sunscreen
NDC: 0363-0261 | Form: LOTION
Manufacturer: WALGREEN COMPANY
Category: otc | Type: HUMAN OTC DRUG LABEL
Date: 20241014

ACTIVE INGREDIENTS: AVOBENZONE 30 mg/1 mL; HOMOSALATE 150 mg/1 mL; OCTOCRYLENE 100 mg/1 mL; OCTISALATE 50 mg/1 mL
INACTIVE INGREDIENTS: EDETATE DISODIUM; CHLORPHENESIN; ETHYLHEXYLGLYCERIN; SILICON DIOXIDE; PEG-100 STEARATE; WATER; WHITE WAX; GLYCERYL 1-STEARATE; ALUMINUM STARCH OCTENYLSUCCINATE; BENZYL ALCOHOL; CAPRYLYL GLYCOL; ETHYLHEXYL STEARATE; POTASSIUM HYDROLYZED JOJOBA ESTERS; JOJOBA OIL; SODIUM POLYACRYLATE (2500000 MW); .ALPHA.-TOCOPHEROL ACETATE; TRIDECETH-6; XANTHAN GUM; CETYL DIMETHICONE 45; DOCOSANOL; BUTYLOCTYL SALICYLATE; CAPRYLYL TRISILOXANE; BUTYL METHACRYLATE/METHYL METHACRYLATE/METHACRYLIC ACID/STYRENE CROSSPOLYMER

Walgreens 70 Sheer Lotion Sunscreen

Active ingredients

Avobenzone 3.0%, Homosalate 15.0%, Octisalate 5.0%, Octocrylene 10.0%

Purpose

Sunscreen

Uses

- helps prevent sunburn
- if used as directed with other sun protection measures (see Directions), decreases the risk of skin cancer and early skin aging caused by the sun

Warnings

For external use only

Do not use

- on damaged or broken skin.

When using this product

keep out of eyes. Rinse with water to remove.

Stop use and ask a doctor if

- rash occurs.

Keep out of reach of children.

If product is swallowed, get medical help or contact a Poison Control Center right away.

Directions

- apply liberally 15 minutes before sun exposure

- reapply:
- after 80 minutes of swimming or sweating
- immediately after towel drying
- at least every 2 hours

- Sun Protection Measures. Spending time in the sun increases your risk of skin cancer and early skin aging. To decrease this risk, regularly use a sunscreen with a Broad Spectrum SPF value of 15 or higher and other sun protection measures including:
- limit time in the sun, especially from 10 a.m.-2 p.m.
- wear long-sleeved shirts, pants, hats, and sunglasses

- children under 6 months: Ask a doctor

Other information

- protect the product in this container from excessive heat and direct sun
- may stain or damage some fabrics, materials or surfaces

Inactive ingredients

acrylates/dimethicone copolymer, aluminum starch octenylsuccinate, beeswax, behenyl alcohol, benzyl alcohol, butyloctyl salicylate, caprylyl glycol, caprylyl methicone, cetyl dimethicone, chlorphenesin, dimethicone, dimethicone/PEG-10/15 crosspolymer, disodium EDTA, ethylhexylglycerin, ethylhexyl stearate, fragrance, glyceryl stearate, hydrolyzed jojoba esters, jojoba esters, PEG-100 stearate, potassium cetyl phosphate, silica, sodium polyacrylate, styrene/acrylates copolymer, tocopheryl acetate,

trideceth-6, water, xanthan gum